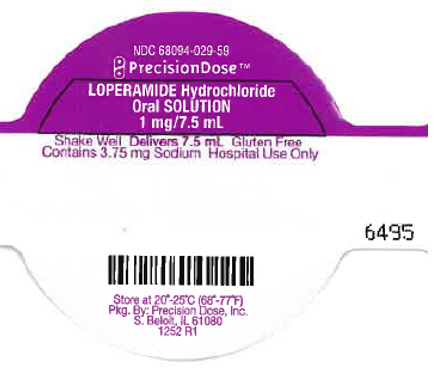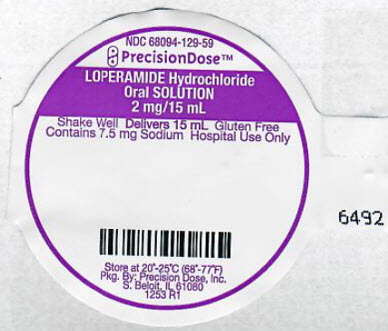 DRUG LABEL: Loperamide Hydrochloride
NDC: 68094-029 | Form: SOLUTION
Manufacturer: Precision Dose, Inc.
Category: otc | Type: HUMAN OTC DRUG LABEL
Date: 20250627

ACTIVE INGREDIENTS: Loperamide Hydrochloride 1 mg/7.5 mL
INACTIVE INGREDIENTS: anhydrous citric acid; carboxymethylcellulose sodium, unspecified; D&C Yellow No. 10; FD&C Blue No. 1; Glycerin; Microcrystalline cellulose; propylene glycol; water; sodium benzoate; sucralose; titanium dioxide; xanthan gum; dimethicone; silicon dioxide

Loperamide Hydrochloride

Mint Flavor

1 mg/7.5 mL 2 mg/15 mL

For Hospital Use Only

Drug Facts

Active ingredient (in each 7.5 mL)

Loperamide HCl 1 mg

Purpose

Anti-diarrheal

Use

controls symptoms of diarrhea, including Travelers' Diarrhea

Read complete directions and warnings before using.

Warnings

Allergy alert

Do not use if you have ever had a rash or other allergic reaction to loperamide HCl

Heart alert

Taking more than directed can cause serious heart problems or death

Do not use if you have bloody or black stool

Ask a doctor before use if you have

- fever
- mucus in the stool
- a history of liver disease

Ask a doctor or pharmacist before use if you are taking antibiotics

When using this product tiredness, drowsiness or dizziness may occur. Be careful when driving or operating machinery.

Stop use and ask a doctor if

- symptoms get worse
- diarrhea lasts for more than 2 days
- you get abdominal swelling or bulging.

These may be signs of a serious condition.

PREGNANCY OR BREAST FEEDING

If pregnant or breast-feeding, ask a health professional before use.

Keep out of reach of children. In case of overdose, get medical help or contact a Poison Control Center right away. (1-800-222-1222)

Directions

- Use as directed per healthcare professional.
- drink plenty of clear fluids to help prevent dehydration caused by diarrhea
- find right dose on chart. If possible, use weight to dose; otherwise use age.
- shake well before using
- mL = milliliter

adults and children 12 years and over | 30 mL after the first loose stool; 15 mL after each subsequent loose stool; but no more than 60 mL in 24 hours
children 9-11 years (60-95 lbs) | 15 mL after the first loose stool; 7.5 mL after each subsequent loose stool; but no more than 45 mL in 24 hours
children 6-8 years (48-59 lbs) | 15 mL after the first loose stool; 7.5 mL after each subsequent loose stool; but no more than 30 mL in 24 hours
children 2-5 years (34 to 47 lbs) | ask a doctor
children under 2 years (up to 33 lbs) | do not use

Other information

- each 30 mL contains: sodium 15 mg
- store between 20-25°C (68-77°F)

Inactive ingredients

anhydrous citric acid, carboxymethylcellulose sodium, D&C yellow no. 10, FD&C blue no. 1, glycerin, microcrystalline cellulose, natural and artificial mint flavor, propylene glycol, purified water, simethicone, sodium benzoate, sucralose, titanium dioxide, xanthan gum

Gluten Free

How Supplied

NDC 68094-029-62
7.5 mL per unit dose cup
Thirty (30) cups per shipper

NDC 68094-129-62
15 mL per unit dose cup
Thirty (30) cups per shipper

Distributed By
Perrigo Company
Allegan, MI 49010

Packaged By
Precision Dose, Inc.
South Beloit, IL 61080

QUESTIONS

For inquiries call Precision Dose, Inc. at 1-800-397-9228 or email druginfo@precisiondose.com

LI1251 Rev. 04/22

PRINCIPAL DISPLAY PANEL - 1 mg/7.5 mL Cup Lid Label

NDC 68094-029-59

PrecisionDose™

LOPERAMIDE Hydrochloride
Oral SOLUTION
1 mg/7.5 mL

Shake Well Delivers 7.5 mL Gluten Free
Contains 3.75 mg Sodium Hospital Use Only

Store at 20°-25°C (68°-77°F)
Pkg. By: Precision Dose, Inc.
S. Beloit, IL 61080
1252 R1

PRINCIPAL DISPLAY PANEL - 2 mg/15 mL Cup Lid Label

NDC 68094-129-59

PrecisionDose™

LOPERAMIDE Hydrochloride
Oral SOLUTION
2 mg/15 mL

Shake Well Delivers 15 mL Gluten Free
Contains 7.5 mg Sodium Hospital Use Only

Store at 20°-25°C (68°-77°F)
Pkg. By: Precision Dose, Inc.
S. Beloit, IL 61080
1253 R1